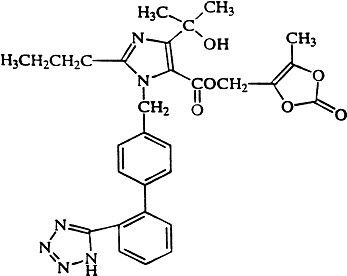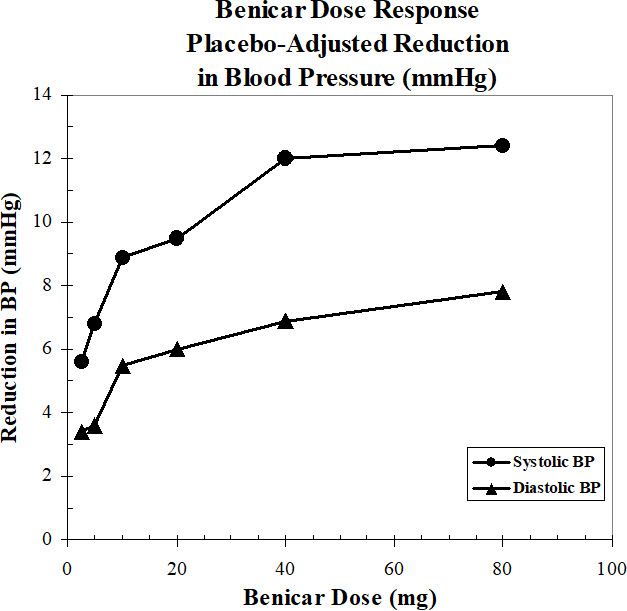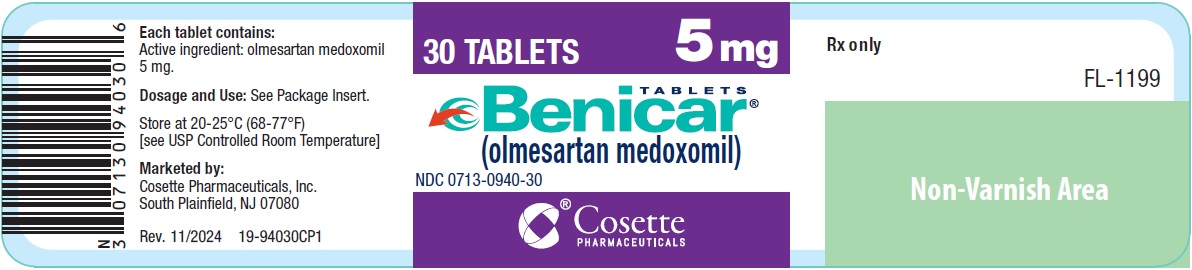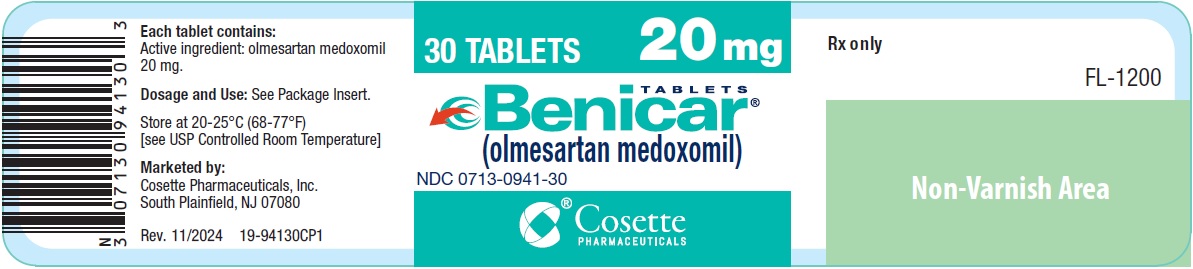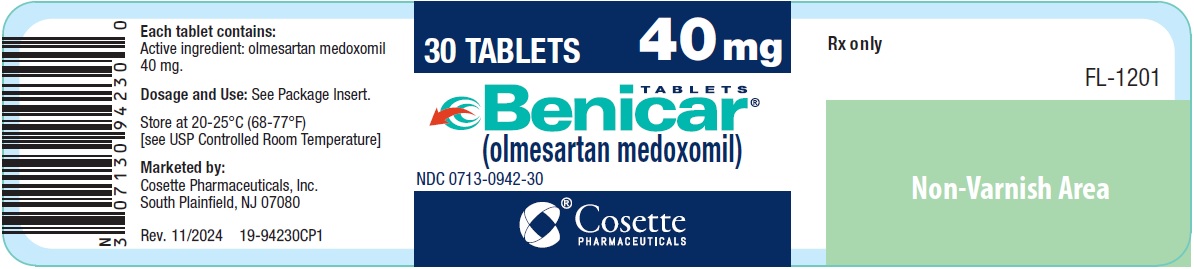 DRUG LABEL: Benicar
NDC: 0713-0940 | Form: TABLET, FILM COATED
Manufacturer: Cosette Pharmaceuticals, Inc.
Category: prescription | Type: HUMAN PRESCRIPTION DRUG LABEL
Date: 20250923

ACTIVE INGREDIENTS: OLMESARTAN MEDOXOMIL 5 mg/1 1
INACTIVE INGREDIENTS: HYDROXYPROPYL CELLULOSE (1600000 WAMW); HYPROMELLOSE, UNSPECIFIED; LACTOSE MONOHYDRATE; LOW-SUBSTITUTED HYDROXYPROPYL CELLULOSE, UNSPECIFIED; MAGNESIUM STEARATE; MICROCRYSTALLINE CELLULOSE; TALC; TITANIUM DIOXIDE; FERRIC OXIDE YELLOW

HIGHLIGHTS OF PRESCRIBING INFORMATION

These highlights do not include all the information needed to use BENICAR safely and effectively. See full prescribing information for BENICAR.
BENICAR (olmesartan medoxomil) tablets, for oral use
Initial U.S. Approval: 2002

WARNING: FETAL TOXICITY

See full prescribing information for complete boxed warning.

- When pregnancy is detected, discontinue Benicar as soon as possible (5.1, 8.1).
- Drugs that act directly on the renin-angiotensin system can cause injury and death to the developing fetus (5.1, 8.1).

1 INDICATIONS AND USAGE

- Benicar is an angiotensin II receptor blocker (ARB) indicated for the treatment of hypertension in adult and pediatric patients six years of age and older, alone or with other antihypertensive agents, to lower blood pressure. Lowering blood pressure reduces the risk of fatal and nonfatal cardiovascular events, primarily strokes and myocardial infarctions (1).

2 DOSAGE AND ADMINISTRATION

Indication | Starting Dose | Dose Range
Adult Hypertension (2.1) | 20 mg once daily | 20 - 40 mg once daily
Pediatric Hypertension (6 years of age and older) (2.2) | 20 to <35 kg | 20 to <35 kg
Pediatric Hypertension (6 years of age and older) (2.2) | 10 mg once daily | 10 - 20 mg once daily
Pediatric Hypertension (6 years of age and older) (2.2) | ≥35 kg | ≥35 kg
Pediatric Hypertension (6 years of age and older) (2.2) | 20 mg once daily | 20 - 40 mg once daily

3 DOSAGE FORMS AND STRENGTHS

Tablets: 5 mg, 20 mg, and 40 mg (3).

4 CONTRAINDICATIONS

Do not co-administer aliskiren with Benicar in patients with diabetes (4).

5 WARNINGS AND PRECAUTIONS

- Avoid fetal (in utero) exposure (5.1).
- Use of Benicar in children <1 year of age is not recommended (5.2).
- Observe for signs and symptoms of hypotension in volume- or salt-depleted patients with treatment initiation (5.3).
- Monitor for worsening renal function in patients with renal impairment (5.4).
- Sprue-like enteropathy has been reported. Consider alternative antihypertensive therapy in cases where no other etiology is found (5.5).

6 ADVERSE REACTIONS

The most common adverse reaction in adults was dizziness (3%) (6.1).

To report SUSPECTED ADVERSE REACTIONS, contact Cosette Pharmaceuticals, Inc. at 1-800-922-1038 or FDA at 1-800-FDA-1088 or www.fda.gov/medwatch.

7 DRUG INTERACTIONS

- Agents increasing potassium levels may lead to increase in serum potassium (7.1).
- NSAID use may lead to increased risk of renal impairment and loss of antihypertensive effect (7.2).
- Dual inhibition of the renin-angiotensin system: Increased risk of renal impairment, hypotension, and hyperkalemia (7.3).
- Lithium: Increases in serum lithium concentrations and lithium toxicity (7.4).
- Colesevelam hydrochloride: Consider administering olmesartan at least 4 hours before colesevelam hydrochloride dose (7.5).

8 USE IN SPECIFIC POPULATIONS

- Lactation: Choose to discontinue nursing or drug (8.2).

FULL PRESCRIBING INFORMATION

WARNING: FETAL TOXICITY

- When pregnancy is detected, discontinue Benicar as soon as possible (5.1, 8.1).
- Drugs that act directly on the renin-angiotensin system can cause injury and death to the developing fetus (5.1, 8.1).

1 INDICATIONS AND USAGE

Benicar is indicated for the treatment of hypertension in adults and children six years of age and older, to lower blood pressure. Lowering blood pressure reduces the risk of fatal and nonfatal cardiovascular events, primarily strokes and myocardial infarctions. These benefits have been seen in controlled trials of antihypertensive drugs from a wide variety of pharmacologic classes including the class to which this drug principally belongs. There are no controlled trials demonstrating risk reduction with Benicar.

Control of high blood pressure should be part of comprehensive cardiovascular risk management, including, as appropriate, lipid control, diabetes management, antithrombotic therapy, smoking cessation, exercise, and limited sodium intake. Many patients will require more than one drug to achieve blood pressure goals. For specific advice on goals and management, see published guidelines, such as those of the National High Blood Pressure Education Program's Joint National Committee on Prevention, Detection, Evaluation, and Treatment of High Blood Pressure (JNC).

Numerous antihypertensive drugs, from a variety of pharmacologic classes and with different mechanisms of action, have been shown in randomized controlled trials to reduce cardiovascular morbidity and mortality, and it can be concluded that it is blood pressure reduction, and not some other pharmacologic property of the drugs, that is largely responsible for those benefits. The largest and most consistent cardiovascular outcome benefit has been a reduction in the risk of stroke, but reductions in myocardial infarction and cardiovascular mortality also have been seen regularly.

Elevated systolic or diastolic pressure causes increased cardiovascular risk, and the absolute risk increase per mmHg is greater at higher blood pressures, so that even modest reductions of severe hypertension can provide substantial benefit. Relative risk reduction from blood pressure reduction is similar across populations with varying absolute risk, so the absolute benefit is greater in patients who are at higher risk independent of their hypertension (for example, patients with diabetes or hyperlipidemia), and such patients would be expected to benefit from more aggressive treatment to a lower blood pressure goal.

Some antihypertensive drugs have smaller blood pressure effects (as monotherapy) in black patients, and many antihypertensive drugs have additional approved indications and effects (e.g., on angina, heart failure, or diabetic kidney disease). These considerations may guide selection of therapy.

It may be used alone or in combination with other antihypertensive agents.

2 DOSAGE AND ADMINISTRATION

2.1 Adult Hypertension

Dosage must be individualized. The usual recommended starting dose of Benicar is 20 mg once daily when used as monotherapy in patients who are not volume-contracted. For patients requiring further reduction in blood pressure after 2 weeks of therapy, the dose of Benicar may be increased to 40 mg. Doses above 40 mg do not appear to have greater effect. Twice-daily dosing offers no advantage over the same total dose given once daily.

For patients with possible depletion of intravascular volume (e.g., patients treated with diuretics, particularly those with impaired renal function), initiate Benicar under close medical supervision and give consideration to use of a lower starting dose [see Warnings and Precautions (5.3)] .

2.2 Pediatric Hypertension (6 Years of Age and Older)

Dosage must be individualized. For children who can swallow tablets, the usual recommended starting dose of Benicar is 10 mg once daily for patients who weigh 20 to <35 kg (44 to 77 lb), or 20 mg once daily for patients who weigh ≥35 kg. For patients requiring further reduction in blood pressure after 2 weeks of therapy, the dose of Benicar may be increased to a maximum of 20 mg once daily for patients who weigh <35 kg or 40 mg once daily for patients who weigh ≥35 kg.

Use of Benicar in children <1 year of age is not recommended [see Warnings and Precautions (5.2) and Use in Specific Populations (8.4)] .

For children who cannot swallow tablets, the same dose can be given using an extemporaneous suspension as described below [see Clinical Pharmacology (12.3)] .

Follow the suspension preparation instructions below to administer Benicar as a suspension.

Preparation of Suspension (for 200 mL of a 2 mg/mL suspension)

Add 50 mL of Purified Water to an amber polyethylene terephthalate (PET) bottle containing twenty Benicar 20 mg tablets and allow to stand for a minimum of 5 minutes. Shake the container for at least 1 minute and allow the suspension to stand for at least 1 minute. Repeat 1-minute shaking and 1-minute standing for four additional times. Add 100 mL of ORA-Sweet® and 50 mL of ORA-Plus®* to the suspension and shake well for at least 1 minute. The suspension should be refrigerated at 2-8°C (36-46°F) and can be stored for up to 4 weeks. Shake the suspension well before each use and return promptly to the refrigerator.

* ORA-Sweet®and ORA-Plus®are registered trademarks of Paddock Laboratories, Inc.

3 DOSAGE FORMS AND STRENGTHS

- 5 mg yellow, round, film-coated, non-scored tablets debossed with C12 on one side and plain on the other side
- 20 mg white, round, film-coated, non-scored tablets debossed with C14 on one side and plain on the other side
- 40 mg white, oval-shaped, film-coated, non-scored tablets debossed with C15 on one side and plain on the other side

4 CONTRAINDICATIONS

Do not co-administer aliskiren with Benicar in patients with diabetes [see Drug Interactions (7.3)].

5 WARNINGS AND PRECAUTIONS

5.1 Fetal Toxicity

Benicar can cause fetal harm when administered to a pregnant woman. Use of drugs that act on the renin-angiotensin system (RAS) during the second and third trimesters of pregnancy reduces fetal renal function and increases fetal and neonatal morbidity and death. Resulting oligohydramnios can be associated with fetal lung hypoplasia and skeletal deformations. Potential neonatal adverse effects include skull hypoplasia, anuria, hypotension, renal failure, and death. When pregnancy is detected, discontinue Benicar as soon as possible [see Use in Specific Populations (8.1)].

5.2 Morbidity in Infants

Use of Benicar in children <1 year of age is not recommended. Drugs that act directly on the renin-angiotensin-aldosterone system (RAAS) can have effects on the development of immature kidneys [see Use in Specific Populations (8.4)].

5.3 Hypotension in Volume- or Salt-Depleted Patients

In patients with an activated renin-angiotensin-aldosterone system, such as volume- and/or salt-depleted patients (e.g., those being treated with high doses of diuretics), symptomatic hypotension may be anticipated after initiation of treatment with Benicar. Initiate treatment under close medical supervision and consider starting at a lower dose. If hypotension does occur, place the patient in the supine position and, if necessary, give an intravenous infusion of normal saline [see Dosage and Administration (2.1)] . A transient hypotensive response is not a contraindication to further treatment, which usually can be continued without difficulty once the blood pressure has stabilized.

5.4 Impaired Renal Function

As a consequence of inhibiting the renin-angiotensin-aldosterone system, changes in renal function may be anticipated in susceptible individuals treated with Benicar. In patients whose renal function may depend upon the activity of the renin-angiotensin-aldosterone system (e.g., patients with severe congestive heart failure), treatment with angiotensin converting enzyme (ACE) inhibitors and angiotensin receptor antagonists has been associated with oliguria and/or progressive azotemia and rarely with acute renal failure and/or death. Similar results may be anticipated in patients treated with Benicar [see Dosage and Administration (2.1), Drug Interactions (7.3), Use in Specific Populations (8.7) and Clinical Pharmacology (12.3)] .

In studies of ACE inhibitors in patients with unilateral or bilateral renal artery stenosis, increases in serum creatinine or blood urea nitrogen (BUN) have been reported. There has been no long-term use of Benicar in patients with unilateral or bilateral renal artery stenosis, but similar results may be expected.

5.5 Sprue-like Enteropathy

Severe, chronic diarrhea with substantial weight loss has been reported in patients taking olmesartan months to years after drug initiation. Intestinal biopsies of patients often demonstrated villous atrophy. If a patient develops these symptoms during treatment with olmesartan, exclude other etiologies. Consider alternative antihypertensive therapy in cases where no other etiology is identified.

5.6 Hyperkalemia

Serum potassium should be monitored in patients receiving Benicar. Drugs that inhibit the renin angiotensin system can cause hyperkalemia. Risk factors for the development of hyperkalemia include renal insufficiency, diabetes mellitus, and the concomitant use of potassium-sparing diuretics, potassium supplements and/or potassium-containing salt substitutes [see Drug Interactions (7.3)] .

6 ADVERSE REACTIONS

6.1 Clinical Trials Experience

Because clinical studies are conducted under widely varying conditions, adverse reaction rates observed in the clinical studies of a drug cannot be directly compared to rates in the clinical studies of another drug and may not reflect the rates observed in practice.

Adult Hypertension

Benicar has been evaluated for safety in more than 3825 patients/subjects, including more than 3275 patients treated for hypertension in controlled trials. This experience included about 900 patients treated for at least 6 months and more than 525 for at least 1 year. Events generally were mild, transient and had no relationship to the dose of Benicar.

Analysis of gender, age and race groups demonstrated no differences between Benicar and placebo-treated patients. The rate of withdrawals due to adverse reactions in all trials of hypertensive patients was 2.4% (i.e., 79/3278) of patients treated with Benicar and 2.7% (i.e., 32/1179) of control patients. In placebo-controlled trials, the only adverse reaction that occurred in more than 1% of patients treated with Benicar and at a higher incidence versus placebo was dizziness (3% vs. 1%).

Facial edema was reported in five patients receiving Benicar. Angioedema has been reported with angiotensin II antagonists.

Pediatric Hypertension

No relevant differences were identified between the adverse experience profile for pediatric patients aged 1 to 16 years and that previously reported for adult patients.

6.2 Post-Marketing Experience

The following adverse reactions have been reported in post-marketing experience. Because these reactions are reported voluntarily from a population of uncertain size, it is not always possible to reliably estimate their frequency or establish a causal relationship to drug exposure.

Body as a Whole: Asthenia, angioedema, anaphylactic reactions

Gastrointestinal: Vomiting, sprue-like enteropathy [see Warnings and Precautions (5.5)]

Metabolic and Nutritional Disorders: Hyperkalemia

Musculoskeletal: Rhabdomyolysis

Urogenital System: Acute renal failure, increased blood creatinine levels

Skin and Appendages: Alopecia, pruritus, urticaria

Data from one controlled trial and an epidemiologic study have suggested that high-dose olmesartan may increase cardiovascular (CV) risk in diabetic patients, but the overall data are not conclusive. The randomized, placebo-controlled, double-blind ROADMAP trial (Randomized Olmesartan And Diabetes MicroAlbuminuria Prevention trial, n=4447) examined the use of olmesartan, 40 mg daily, vs. placebo in patients with type 2 diabetes mellitus, normoalbuminuria, and at least one additional risk factor for CV disease. The trial met its primary endpoint, delayed onset of microalbuminuria, but olmesartan had no beneficial effect on decline in glomerular filtration rate (GFR). There was a finding of increased CV mortality (adjudicated sudden cardiac death, fatal myocardial infarction, fatal stroke, revascularization death) in the olmesartan group compared to the placebo group (15 olmesartan vs. 3 placebo, HR 4.9, 95% confidence interval [CI], 1.4, 17), but the risk of non-fatal myocardial infarction was lower with olmesartan (HR 0.64, 95% CI 0.35, 1.18).

The epidemiologic study included patients 65 years and older with overall exposure of > 300,000 patient-years. In the sub-group of diabetic patients receiving high-dose olmesartan (40 mg/d) for > 6 months, there appeared to be an increased risk of death (HR 2.0, 95% CI 1.1, 3.8) compared to similar patients taking other angiotensin receptor blockers. In contrast, high-dose olmesartan use in non-diabetic patients appeared to be associated with a decreased risk of death (HR 0.46, 95% CI 0.24, 0.86) compared to similar patients taking other angiotensin receptor blockers. No differences were observed between the groups receiving lower doses of olmesartan compared to other angiotensin blockers or those receiving therapy for < 6 months.

Overall, these data raise a concern of a possible increased CV risk associated with the use of high-dose olmesartan in diabetic patients. There are, however, concerns with the credibility of the finding of increased CV risk, notably the observation in the large epidemiologic study for a survival benefit in non-diabetics of a magnitude similar to the adverse finding in diabetics.

7 DRUG INTERACTIONS

7.1 Agents Increasing Serum Potassium

Concomitant use of olmesartan with other agents that block the renin-angiotensin system, potassium-sparing diuretics (e.g., spironolactone, triamterene, amiloride), potassium supplements, salt substitutes containing potassium or other drugs that may increase potassium levels (e.g., heparin) may lead to increases in serum potassium. If co-medication is considered necessary, monitoring of serum potassium is advisable.

7.2 Non-Steroidal Anti-Inflammatory Agents Including Selective Cyclooxygenase-2 Inhibitors (COX-2 Inhibitors)

In patients who are elderly, volume-depleted (including those on diuretic therapy), or with compromised renal function, co-administration of NSAIDs, including selective COX-2 inhibitors, with angiotensin II receptor antagonists, including olmesartan medoxomil, may result in deterioration of renal function, including possible acute renal failure. These effects are usually reversible. Monitor renal function periodically in patients receiving olmesartan medoxomil and NSAID therapy.

The antihypertensive effect of angiotensin II receptor antagonists, including olmesartan medoxomil, may be attenuated by NSAIDs including selective COX-2 inhibitors.

7.3 Dual Blockade of the Renin-Angiotensin System (RAS)

Dual blockade of the RAS with angiotensin receptor blockers, ACE inhibitors, or aliskiren is associated with increased risks of hypotension, hyperkalemia, and changes in renal function (including acute renal failure) compared to monotherapy. Most patients receiving the combination of two RAS inhibitors do not obtain any additional benefit compared to monotherapy. In general, avoid combined use of RAS inhibitors. Closely monitor blood pressure, renal function and electrolytes in patients on Benicar and other agents that affect the RAS.

Do not co-administer aliskiren with Benicar in patients with diabetes [see Contraindications (4)]. Avoid use of aliskiren with Benicar in patients with renal impairment (GFR <60 ml/min).

7.4 Lithium

Increases in serum lithium concentrations and lithium toxicity have been reported during concomitant administration of lithium with angiotensin II receptor antagonists, including BENICAR. Monitor serum lithium levels during concomitant use.

7.5 Colesevelam Hydrochloride

Concurrent administration of bile acid sequestering agent colesevelam hydrochloride reduces the systemic exposure and peak plasma concentration of olmesartan. Administration of olmesartan at least 4 hours prior to colesevelam hydrochloride decreased the drug interaction effect. Consider administering olmesartan at least 4 hours before the colesevelam hydrochloride dose [see Clinical Pharmacology (12.3)] .

8 USE IN SPECIFIC POPULATIONS

8.1 Pregnancy

Risk Summary

Benicar can cause fetal harm when administered to a pregnant woman. Use of drugs that act on the renin-angiotensin system during the second and third trimesters of pregnancy reduces fetal renal function and increases fetal and neonatal morbidity and death. Most epidemiologic studies examining fetal abnormalities after exposure to antihypertensive use in the first trimester have not distinguished drugs affecting the renin-angiotensin system from other antihypertensive agents. In animal reproduction studies, Benicar treatment during organogenesis resulted in increased embryofetal toxicity in rats at doses lower than maternally toxic doses.

When pregnancy is detected, discontinue Benicar as soon as possible. Consider alternative antihypertensive therapy during pregnancy.

The estimated background risk of major birth defects and miscarriage for the indicated population is unknown. All pregnancies have a background risk of birth defect, loss or other adverse outcomes. In the U.S. general population, the estimated background risk of major birth defects and miscarriage in clinically recognized pregnancies is 2%–4% and 15%–20%, respectively.

Clinical Considerations

Disease-Associated Maternal and/or Embryo/Fetal Risk

Hypertension in pregnancy increases the maternal risk for pre-eclampsia, gestational diabetes, premature delivery, and delivery complications (e.g., need for cesarean section and post-partum hemorrhage). Hypertension increases the fetal risk for intrauterine growth restriction and intrauterine death. Pregnant women with hypertension should be carefully monitored and managed accordingly.

Fetal/Neonatal Adverse Reactions

Oligohydramnios in pregnant women who use drugs affecting the renin-angiotensin system in the second and third trimesters of pregnancy can result in the following: reduced fetal renal function leading to anuria and renal failure, fetal lung hypoplasia, skeletal deformations, including skull hypoplasia, hypotension and death.

In patients taking Benicar during pregnancy, perform serial ultrasound examinations to assess the intra-amniotic environment. Fetal testing may be appropriate, based on the week of gestation. Patients and physicians should be aware, however, that oligohydramnios may not appear until after the fetus has sustained irreversible injury.

Closely observe infants with histories of in utero exposure to Benicar for hypotension, oliguria, and hyperkalemia. In neonates with a history of in utero exposure to Benicar, if oliguria or hypotension occurs, utilize measures to maintain adequate blood pressure and renal perfusion. Exchange transfusions or dialysis may be required as a means of reversing hypotension and supporting renal function.

Data

Animal Data

No teratogenic effects were observed when olmesartan medoxomil was administered to pregnant rats at oral doses up to 1000 mg/kg/day (240 times the maximum recommended human dose (MRHD) on a mg/m^2 basis) or pregnant rabbits at oral doses up to 1 mg/kg/day (half the MRHD on a mg/m^2 basis; higher doses could not be evaluated for effects on fetal development as they were lethal to the does). In rats, significant decreases in pup birth weight and weight gain were observed at doses ≥1.6 mg/kg/day, and delays in developmental milestones (delayed separation of ear auricula, eruption of lower incisors, appearance of abdominal hair, descent of testes, and separation of eyelids) and dose-dependent increases in the incidence of dilation of the renal pelvis were observed at doses ≥ 8 mg/kg/day. The no observed effect dose for developmental toxicity in rats is 0.3 mg/kg/day, about one-tenth the MRHD of 40 mg/day.

8.2 Lactation

Risk Summary

There is no information regarding the presence of olmesartan in human milk, the effects on the breastfed infant, or the effects on milk production. Olmesartan is secreted at low concentration in the milk of lactating rats (see Data) . Because of the potential for adverse effects on the nursing infant, a decision should be made whether to discontinue nursing or discontinue the drug, taking into account the importance of the drug to the mother.

Data

Presence of olmesartan in milk was observed after a single oral administration of 5 mg/kg [^14C] olmesartan medoxomil to lactating rats.

8.4 Pediatric Use

The antihypertensive effects of Benicar were evaluated in one randomized, double-blind clinical study in pediatric patients 1 to 16 years of age [see Clinical Studies (14.2)] . The pharmacokinetics of Benicar were evaluated in pediatric patients 1 to 16 years of age [see Clinical Pharmacology (12.3)] . Benicar was generally well tolerated in pediatric patients, and the adverse experience profile was similar to that described for adults.

Benicar has not been shown to be effective for hypertension in children <6 years of age.

Use of Benicar in children <1 year of age is not recommended [see Warnings and Precautions (5.2)] . The renin-angiotensin-aldosterone system (RAAS) plays a critical role in kidney development. RAAS blockade has been shown to lead to abnormal kidney development in very young mice. Administering drugs that act directly on the renin- angiotensin aldosterone system (RAAS) can alter normal renal development.

8.5 Geriatric Use

Of the total number of hypertensive patients receiving Benicar in clinical studies, more than 20% were 65 years of age and over, while more than 5% were 75 years of age and older. No overall differences in effectiveness or safety were observed between elderly patients and younger patients. Other reported clinical experience has not identified differences in responses between the elderly and younger patients, but greater sensitivity of some older individuals cannot be ruled out [see Clinical Pharmacology (12.3)] .

8.6 Hepatic Impairment

Increases in AUC0-∞ and Cmax were observed in patients with moderate hepatic impairment compared to those in matched controls, with an increase in AUC of about 60%. No initial dosage adjustment is recommended for patients with moderate to marked hepatic dysfunction [see Clinical Pharmacology (12.3)] .

8.7 Renal Impairment

Patients with renal insufficiency have elevated serum concentrations of olmesartan compared to subjects with normal renal function. After repeated dosing, the AUC was approximately tripled in patients with severe renal impairment (creatinine clearance <20 mL/min). No initial dosage adjustment is recommended for patients with moderate to marked renal impairment (creatinine clearance <40 mL/min) [see Dosage and Administration (2.1), Warnings and Precautions (5.4) and Clinical Pharmacology (12.3)] .

8.8 Black Patients

The antihypertensive effect of Benicar was smaller in black patients (usually a low-renin population), as has been seen with ACE inhibitors, beta-blockers and other angiotensin receptor blockers.

10 OVERDOSAGE

Limited data are available related to overdosage in humans. The most likely manifestations of overdosage would be hypotension and tachycardia; bradycardia could be encountered if parasympathetic (vagal) stimulation occurs. If symptomatic hypotension occurs, initiate supportive treatment. The dialyzability of olmesartan is unknown.

11 DESCRIPTION

Olmesartan medoxomil, a prodrug, is hydrolyzed to olmesartan during absorption from the gastrointestinal tract. Olmesartan is a selective AT1 subtype angiotensin II receptor antagonist.

Olmesartan medoxomil is described chemically as 2,3-dihydroxy-2-butenyl 4-(1-hydroxy-1-methylethyl)-2-propyl-1-[ p-(o-1 H-tetrazol-5-ylphenyl)benzyl]imidazole-5-carboxylate, cyclic 2,3-carbonate.

Its empirical formula is C29H30N6O6 and its structural formula is:

Olmesartan medoxomil is a white to light yellowish-white powder or crystalline powder with a molecular weight of 558.59. It is practically insoluble in water and sparingly soluble in methanol. Benicar is available for oral use as film-coated tablets containing 5 mg, 20 mg, or 40 mg of olmesartan medoxomil and the following inactive ingredients: hydroxypropyl cellulose, hypromellose, lactose monohydrate, low-substituted hydroxypropyl cellulose, magnesium stearate, microcrystalline cellulose, talc, titanium dioxide, and (5 mg only) yellow iron oxide.

12 CLINICAL PHARMACOLOGY

12.1 Mechanism of Action

Angiotensin II is formed from angiotensin I in a reaction catalyzed by angiotensin converting enzyme (ACE, kininase II). Angiotensin II is the principal pressor agent of the renin-angiotensin system, with effects that include vasoconstriction, stimulation of synthesis and release of aldosterone, cardiac stimulation and renal reabsorption of sodium. Olmesartan blocks the vasoconstrictor effects of angiotensin II by selectively blocking the binding of angiotensin II to the AT1 receptor in vascular smooth muscle. Its action is, therefore, independent of the pathways for angiotensin II synthesis.

An AT2 receptor is found also in many tissues, but this receptor is not known to be associated with cardiovascular homeostasis. Olmesartan has more than a 12,500-fold greater affinity for the AT1 receptor than for the AT2 receptor.

Blockade of the renin-angiotensin system with ACE inhibitors, which inhibit the biosynthesis of angiotensin II from angiotensin I, is a mechanism of many drugs used to treat hypertension. ACE inhibitors also inhibit the degradation of bradykinin, a reaction also catalyzed by ACE. Because olmesartan medoxomil does not inhibit ACE (kininase II), it does not affect the response to bradykinin. Whether this difference has clinical relevance is not yet known.

Blockade of the angiotensin II receptor inhibits the negative regulatory feedback of angiotensin II on renin secretion, but the resulting increased plasma renin activity and circulating angiotensin II levels do not overcome the effect of olmesartan on blood pressure.

12.2 Pharmacodynamics

Benicar doses of 2.5 mg to 40 mg inhibit the pressor effects of angiotensin I infusion. The duration of the inhibitory effect was related to dose, with doses of Benicar >40 mg giving >90% inhibition at 24 hours.

Plasma concentrations of angiotensin I and angiotensin II and plasma renin activity (PRA) increase after single and repeated administration of Benicar to healthy subjects and hypertensive patients. Repeated administration of up to 80 mg Benicar had minimal influence on aldosterone levels and no effect on serum potassium.

12.3 Pharmacokinetics

Absorption

Olmesartan medoxomil is rapidly and completely bioactivated by ester hydrolysis to olmesartan during absorption from the gastrointestinal tract.

Benicar tablets and the suspension formulation prepared from Benicar tablets are bioequivalent [see Dosage and Administration (2.2)] .

The absolute bioavailability of olmesartan is approximately 26%. After oral administration, the peak plasma concentration (Cmax) of olmesartan is reached after 1 to 2 hours. Food does not affect the bioavailability of olmesartan. Benicar may be administered with or without food.

Distribution

The volume of distribution of olmesartan is approximately 17 L. Olmesartan is highly bound to plasma proteins (99%) and does not penetrate red blood cells. The protein binding is constant at plasma olmesartan concentrations well above the range achieved with recommended doses.

In rats, olmesartan crossed the blood-brain barrier poorly, if at all. Olmesartan passed across the placental barrier in rats and was distributed to the fetus. Olmesartan was distributed to milk at low levels in rats.

Metabolism and Excretion

Following the rapid and complete conversion of olmesartan medoxomil to olmesartan during absorption, there is virtually no further metabolism of olmesartan. Total plasma clearance of olmesartan is 1.3 L/h, with a renal clearance of 0.6 L/h. Approximately 35% to 50% of the absorbed dose is recovered in urine while the remainder is eliminated in feces via the bile.

Olmesartan appears to be eliminated in a biphasic manner with a terminal elimination half-life of approximately 13 hours. Olmesartan shows linear pharmacokinetics following single oral doses of up to 320 mg and multiple oral doses of up to 80 mg. Steady-state levels of olmesartan are achieved within 3 to 5 days and no accumulation in plasma occurs with once-daily dosing.

Specific Populations

Geriatric Patients

The pharmacokinetics of olmesartan were studied in the elderly (≥65 years). Overall, maximum plasma concentrations of olmesartan were similar in young adults and the elderly. Modest accumulation of olmesartan was observed in the elderly with repeated dosing; AUCss,τ was 33% higher in elderly patients, corresponding to an approximate 30% reduction in CLR [see Dosage and Administration (2.1) and Use in Specific Populations (8.5)] .

Pediatric Patients

The pharmacokinetics of olmesartan were studied in pediatric hypertensive patients aged 1 to 16 years. The clearance of olmesartan in pediatric patients was similar to that in adult patients when adjusted by the body weight [see Use in Specific Populations (8.4)] .

Olmesartan pharmacokinetics have not been investigated in pediatric patients less than 1 year of age [see Warnings and Precautions (5.2) and Use in Specific Populations (8.4)].

Male and Female Patients

Minor differences were observed in the pharmacokinetics of olmesartan in women compared to men. AUC and Cmax were 10-15% higher in women than in men.

Patients with Hepatic Impairment

Increases in AUC0-∞ and Cmax were observed in patients with moderate hepatic impairment compared to those in matched controls, with an increase in AUC of about 60% [see Dosage and Administration (2.1) and Use in Specific Populations (8.6)] .

Patients with Renal Impairment

In patients with renal insufficiency, serum concentrations of olmesartan were elevated compared to subjects with normal renal function. After repeated dosing, the AUC was approximately tripled in patients with severe renal impairment (creatinine clearance <20 mL/min). The pharmacokinetics of olmesartan in patients undergoing hemodialysis has not been studied [see Dosage and Administration (2.1), Warnings and Precautions (5.4) and Use in Specific Populations (8.7)] .

Drug Interaction Studies

Bile Acid Sequestering Agent Colesevelam

Concomitant administration of 40 mg olmesartan medoxomil and 3750 mg colesevelam hydrochloride in healthy subjects resulted in 28% reduction in Cmax and 39% reduction in AUC of olmesartan. Lesser effects, 4% and 15% reduction in Cmax and AUC respectively, were observed when olmesartan medoxomil was administered 4 hours prior to colesevelam hydrochloride [see Drug Interactions (7.5)] .

Other Studies

No significant drug interactions were reported in studies in which olmesartan medoxomil was co-administered with digoxin or warfarin in healthy volunteers.

The bioavailability of olmesartan was not significantly altered by the co-administration of antacids [Al(OH)3/Mg(OH)2].

Olmesartan medoxomil is not metabolized by the cytochrome P450 system and has no effects on P450 enzymes; thus, interactions with drugs that inhibit, induce, or are metabolized by those enzymes are not expected.

13 NONCLINICAL TOXICOLOGY

13.1 Carcinogenesis, Mutagenesis, Impairment of Fertility

Olmesartan medoxomil was not carcinogenic when administered by dietary administration to rats for up to 2 years. The highest dose tested (2000 mg/kg/day) was, on a mg/m^2 basis, about 480 times the maximum recommended human dose (MRHD) of 40 mg/day. Two carcinogenicity studies conducted in mice, a 6-month gavage study in the p53 knockout mouse and a 6-month dietary administration study in the Hras2 transgenic mouse, at doses of up to 1000 mg/kg/day (about 120 times the MRHD), revealed no evidence of a carcinogenic effect of olmesartan medoxomil.

Both olmesartan medoxomil and olmesartan tested negative in the in vitro Syrian hamster embryo cell transformation assay and showed no evidence of genetic toxicity in the Ames (bacterial mutagenicity) test. However, both were shown to induce chromosomal aberrations in cultured cells in vitro (Chinese hamster lung) and tested positive for thymidine kinase mutations in the in vitro mouse lymphoma assay. Olmesartan medoxomil tested negative in vivo for mutations in the MutaMouse intestine and kidney and for clastogenicity in mouse bone marrow (micronucleus test) at oral doses of up to 2000 mg/kg (olmesartan not tested).

Fertility of rats was unaffected by administration of olmesartan medoxomil at dose levels as high as 1000 mg/kg/day (240 times the MRHD) in a study in which dosing was begun 2 (female) or 9 (male) weeks prior to mating.

14 CLINICAL STUDIES

14.1 Adult Hypertension

The antihypertensive effects of Benicar have been demonstrated in seven placebo-controlled studies at doses ranging from 2.5 mg to 80 mg for 6 to 12 weeks, each showing statistically significant reductions in peak and trough blood pressure. A total of 2693 patients (2145 Benicar; 548 placebo) with essential hypertension were studied. Benicar once daily lowered diastolic and systolic blood pressure. The response was dose related, as shown in the following graph. A Benicar dose of 20 mg daily produces a trough sitting blood pressure (BP) reduction over placebo of about 10/6 mmHg and a dose of 40 mg daily produces a trough sitting BP reduction over placebo of about 12/7 mmHg. Benicar doses greater than 40 mg had little additional effect. The onset of the antihypertensive effect occurred within 1 week and was largely manifest after 2 weeks.

Data above are from seven placebo-controlled studies (2145 Benicar patients, 548 placebo patients). The blood pressure lowering effect was maintained throughout the 24-hour period with Benicar once daily, with trough-to-peak ratios for systolic and diastolic response between 60 and 80%.

The blood pressure lowering effect of Benicar, with and without hydrochlorothiazide, was maintained in patients treated for up to 1 year. There was no evidence of tachyphylaxis during long-term treatment with Benicar or rebound effect following abrupt withdrawal of olmesartan medoxomil after 1 year of treatment.

The antihypertensive effect of Benicar was similar in men and women and in patients older and younger than 65 years. The effect was smaller in black patients (usually a low-renin population), as has been seen with ACE inhibitors, beta-blockers and other angiotensin receptor blockers. Benicar had an additional blood pressure lowering effect when added to hydrochlorothiazide.

There are no trials of Benicar demonstrating reductions in cardiovascular risk in patients with hypertension, but at least one pharmacologically similar drug has demonstrated such benefits.

14.2 Pediatric Hypertension

The antihypertensive effects of Benicar in the pediatric population were evaluated in a randomized, double-blind study involving 302 hypertensive patients aged 6 to 16 years. The study population consisted of an all-black cohort of 112 patients and a mixed racial cohort of 190 patients, including 38 black patients. The etiology of the hypertension was predominantly essential hypertension (87% of the black cohort and 67% of the mixed cohort). Patients who weighed 20 to <35 kg were randomized to 2.5 or 20 mg of Benicar once daily and patients who weighed ≥35 kg were randomized to 5 or 40 mg of Benicar once daily. At the end of 3 weeks, patients were re-randomized to continuing Benicar or to taking placebo for up to 2 weeks. During the initial dose-response phase, Benicar significantly reduced both systolic and diastolic blood pressure in a weight-adjusted, dose-dependent manner. Overall, the two dose levels of Benicar (low and high) significantly reduced systolic blood pressure by 6.6 and 11.9 mmHg from the baseline, respectively. These reductions in systolic blood pressure included both drug and placebo effect. During the randomized withdrawal to placebo phase, mean systolic blood pressure at trough was 3.2 mmHg lower and mean diastolic blood pressure at trough was 2.8 mmHg lower in patients continuing Benicar than in patients withdrawn to placebo. These differences were statistically different. As observed in adult populations, the blood pressure reductions were smaller in black patients.

In the same study, 59 patients aged 1 to 5 years who weighed ≥5 kg received 0.3 mg/kg of Benicar once daily for three weeks in an open-label phase and then were randomized to receiving Benicar or placebo in a double-blind phase. At the end of the second week of withdrawal, the mean systolic/diastolic blood pressure at trough was 3/3 mmHg lower in the group randomized to Benicar; this difference in blood pressure was not statistically significant (95% C.I. -2 to 7/-1 to 7).

16 HOW SUPPLIED/STORAGE AND HANDLING

Benicar is supplied as yellow, round, film-coated, non-scored tablets containing 5 mg of olmesartan medoxomil, as white, round, film-coated, non-scored tablets containing 20 mg of olmesartan medoxomil, and as white, oval-shaped, film-coated, non-scored tablets containing 40 mg of olmesartan medoxomil. Tablets are debossed with C12, C14, or C15 on one side and plain on the other side of the 5, 20, and 40 mg tablets, respectively.

Tablets are supplied as follows:

 | 5 mg | 20 mg | 40 mg
Bottle of 30 | NDC 0713-0940-30 | NDC 0713-0941-30 | NDC 0713-0942-30
Bottle of 90 | Not available | Not available | Not available
Blister 10 cards × 10 | Not available | Not available | Not available
Blister 1 card × 30 | Not available | Not available | Not available
Carton of 6 cards × 30 | Not available | Not available | Not available

Storage

Store at 20-25°C (68-77°F) [see USP Controlled Room Temperature].

17 PATIENT COUNSELING INFORMATION

Pregnancy: Advise female patients of childbearing age about the consequences of exposure to Benicar during pregnancy. Discuss treatment options with women planning to become pregnant. Tell patients to report pregnancies to their physicians as soon as possible [see Warnings and Precautions (5.1) and Use in Specific Populations (8.1)] .

Lactation: Advise nursing women not to breastfeed during treatment with BENICAR [see Use in Specific Populations (8.2)] .

Hyperkalemia: Advise patients not to use potassium supplements or salt substitutes that contain potassium without consulting their healthcare provider [see Drug Interactions (7.1)] .

Marketed by Cosette Pharmaceuticals, Inc. South Plainfield, NJ 07080

Rx Only

8-BEOCP1

PRINCIPAL DISPLAY PANEL

NDC 0713-0940-30
TABLETS
Benicar
(olmesartan medoxomil)
5 mg
30 TABLETS
Rx only

PRINCIPAL DISPLAY PANEL

NDC 0713-0941-30
TABLETS
Benicar
(olmesartan medoxomil)
20 mg
30 TABLETS
Rx only

PRINCIPAL DISPLAY PANEL

NDC 0713-0942-30
TABLETS
Benicar
(olmesartan medoxomil)
40 mg
30 TABLETS
Rx only